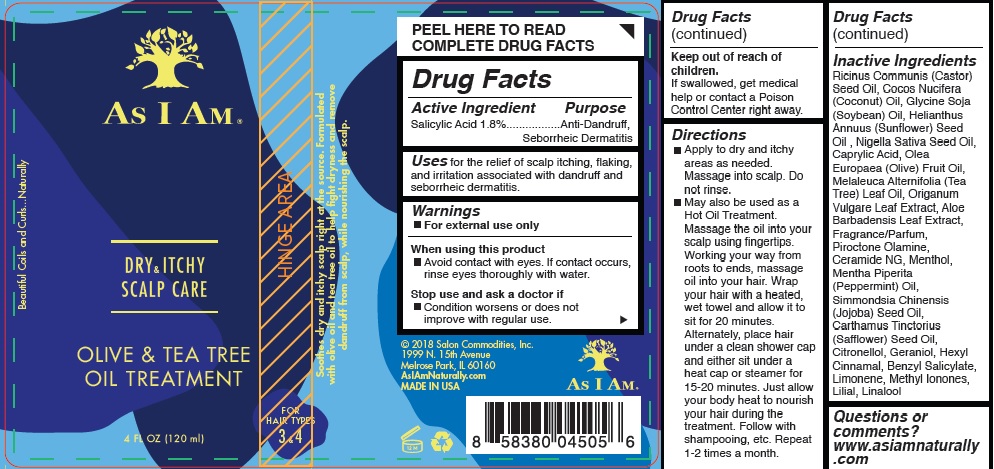 DRUG LABEL: As I Am
NDC: 72474-102 | Form: OIL
Manufacturer: Salon Commodities, Inc.
Category: otc | Type: HUMAN OTC DRUG LABEL
Date: 20241009

ACTIVE INGREDIENTS: SALICYLIC ACID 18 mg/1 mL
INACTIVE INGREDIENTS: BUTYLPHENYL METHYLPROPIONAL; CASTOR OIL; ALOE VERA LEAF; COCONUT OIL; GERANIOL; LINALOOL, (+/-)-; SOYBEAN; SUNFLOWER OIL; NIGELLA SATIVA SEED OIL; OLIVE OIL; TEA TREE OIL; PEPPERMINT OIL; JOJOBA OIL; SAFFLOWER OIL; BENZYL SALICYLATE; PIROCTONE OLAMINE; CERAMIDE NG; CAPRYLIC ACID; LIMONENE, (+)-; METHYL IONONES; MENTHOL; OREGANO; .BETA.-CITRONELLOL, (R)-; .ALPHA.-HEXYLCINNAMALDEHYDE

As I Am - Dry & Itchy Scalp Care - Olive and Tea Tree Oil Treatment

Active Ingredient

Salicylic Acid 1.8%

Purpose

Anti-Dandruff, Seborrheic Dermatitis

Uses

For the relief of scalp itching, flaking, and irritation associated with dandruff and seborrheic dermatitis.

Warnings

- For external use only.

When Using This Product

- Avoid contact with eyes. If contact occurs, rinse eyes thoroughly with water.

Stop use and ask a doctor if

- Condition worsens or does not improve with regular use.

Keep out of reach of children. If swallowed, get medical help or contact a Poison Control Center right away.

Directions

- Apply to dry and itchy areas as needed. Massage into scalp. Do not rinse.
- May also be used as a Hot Oil Treatment. Massage the oil into your scalp using fingertips. Working your way from roots to ends, massage oil into your hair. Wrap your hair with a heated, wet towel and allow it to sit for 20 minutes. Alternately, place hair under a clean shower cap and either sit under a heat cap or steamer for 15-20 minutes. Just allow your body heat to nourish your hair during the treatment. Follow with shampooing, etc. Repeat 1-2 times a month.

Inactive Ingredient

Ricinus Communis (Castor) Seed Oil, Cocos Nucifera (Coconut) Oil, Glycine Soja (Soybean) Oil, Helianthus Annuus (Sunflower) Seed Oil , Nigella Sativa Seed Oil, Caprylic Acid, Olea Europaea (Olive) Fruit Oil, Melaleuca Alternifolia (Tea Tree) Leaf Oil, Origanum Vulgare Leaf Extract, Aloe Barbadensis Leaf Extract, Fragrance/Parfum, Piroctone Olamine, Ceramide NG, Menthol, Mentha Piperita
(Peppermint) Oil, Simmondsia Chinensis (Jojoba) Seed Oil, Carthamus Tinctorius (Safflower) Seed Oil, Citronellol, Geraniol, Hexyl Cinnamal, Benzyl Salicylate, Limonene, Methyl Ionones, Lilial, Linalool

Questions or comments? www.asiamnaturally.com

PACKAGE LABEL

As I Am - Dry & Itchy Scalp Care - Olive and Tea Tree Oil Treatment

4 FL OZ (120 ml)

NDC 72474-102-01